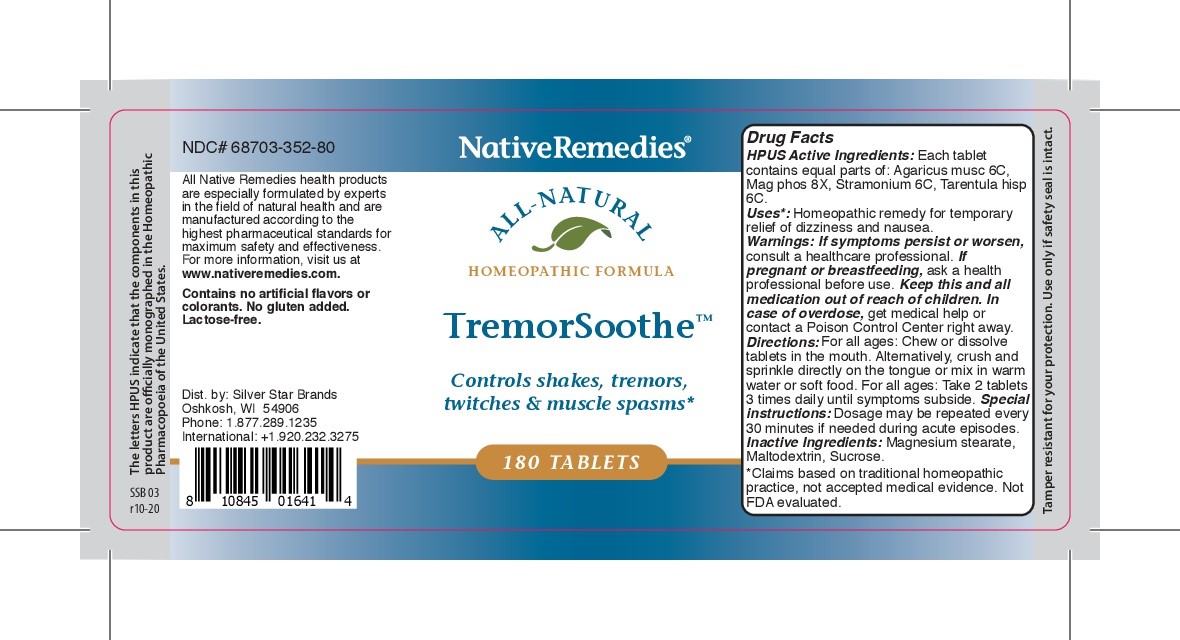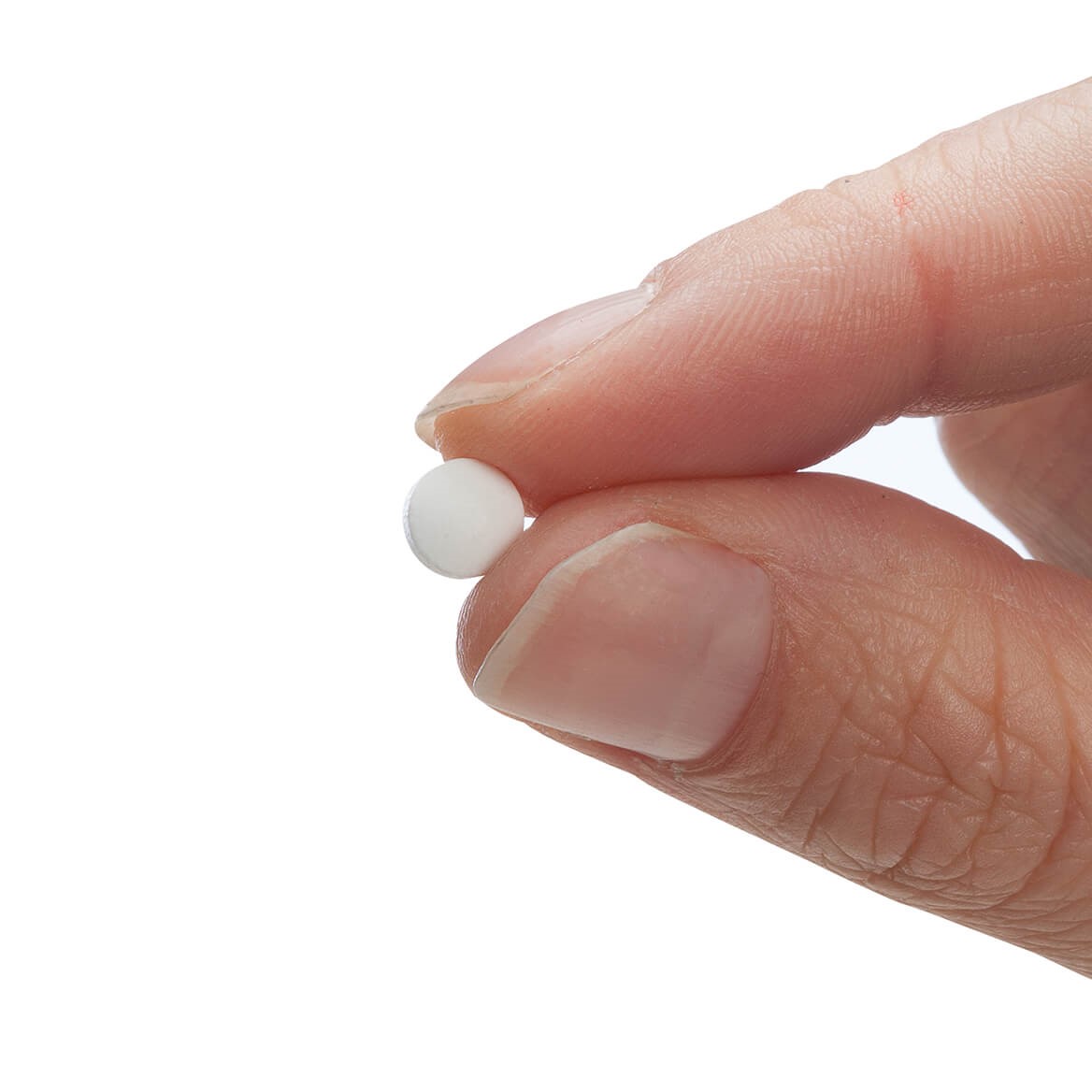 DRUG LABEL: TremorSoothe
NDC: 68703-352 | Form: TABLET
Manufacturer: Silver Star Brands
Category: homeopathic | Type: HUMAN OTC DRUG LABEL
Date: 20250101

ACTIVE INGREDIENTS: AMANITA MUSCARIA FRUITING BODY 6 [hp_C]/180 1; MAGNESIUM PHOSPHATE, DIBASIC TRIHYDRATE 8 [hp_X]/180 1; LYCOSA TARANTULA 6 [hp_C]/180 1; DATURA STRAMONIUM 6 [hp_C]/180 1
INACTIVE INGREDIENTS: SUCROSE; MAGNESIUM STEARATE; MALTODEXTRIN

NativeRemedies® TremorSoothe™ Tablets

HPUS Active Ingredients: Each tablet contains equal parts of Agaricus musc 6C, Mag phos 8X, Stramonium 6C, Tarentula hisp 6C.

Uses*:

Uses*: Homeopathic remedy for temporary relief of dizziness and nausea.

*Clais based on traditional homeopatchi practice, not accepted medical evidence. Not FDA evaluated.

Uses*:

Uses*:Homeopathic remedy for temporary relief of dizziness and nausea.

*Claims based on traditional homeopathic practice, not accepted medical evidence. Not FDA evaluated.

Warnings

Warnings: If symptoms persist or worsen, consult a healthcare professional. If pregnant or breastfeeding, ask a health professional before use. Keep this and all medication out of reach of children. in case of overdose, get medical help or contact a Poison Control Center right away.

Directions

Directions: For all ages: Chew or dissolve tablets in the mouth. Alternatively, crush and sprinkle directly on the tongue or mix in warm water or soft food. For all ages: Take 2 tablets 3 times daily until symptoms subside.

Special instructions: Dosage may be repeated every 30 minutes if needed during acute episodes.

OTHER SAFETY INFORMATION

Contains no artificial flavors or colorants. No gluten added. Lactose-free.

Tamper resistant for your protection. Use only if safety seal is intact.

Inactive Ingredients

Inactive Ingredients: Magnesium stearate, Maltodextrin, Sucrose.

KEEP OUT OF REACH OF CHILDREN

Keep this and all medication our of reach of children.

PREGNANCY OR BREAST FEEDING

If pregnant or breastfeeding, ask a healthcare professional before use.

PURPOSE

Controls shakes, tremors, twitches & muscle spasms*

*Claims based on traditional homeopathic practice, not acceptd medical evidence. Not FDA evaluated.